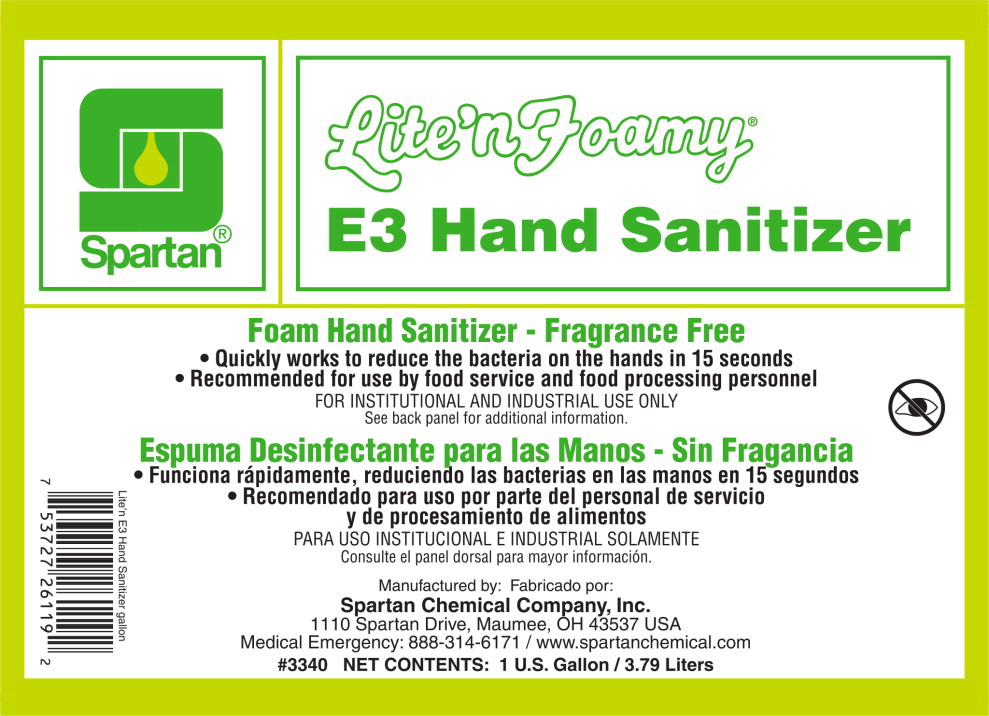 DRUG LABEL: Lite nFoamy E3 Hand Sanitizer
NDC: 64009-334 | Form: SOAP
Manufacturer: Spartan Chemical Company
Category: otc | Type: HUMAN OTC DRUG LABEL
Date: 20231219

ACTIVE INGREDIENTS: BENZALKONIUM CHLORIDE 1 g/1 L
INACTIVE INGREDIENTS: WATER; CETRIMONIUM CHLORIDE; LAURTRIMONIUM CHLORIDE; COCAMIDOPROPYL PROPYLENE GLYCOL-DIMONIUM CHLORIDE PHOSPHATE; DIHYDROXYETHYL COCAMINE OXIDE; CITRIC ACID MONOHYDRATE

Drug Facts

Active Ingredients

Benzalkonium Chloride 0.1%

Purpose

Antimicrobial

Uses

- For hand sanitizing to decrease bacteria on the skin.
- Recommended for repeated use.

Warnings

- For external use only

When using this product avoid contact with eyes. In case of eye contact, flush eyes with water.

Stop use and ask a doctor if irritation and redness develops, or if condition persists for more than 72 hours.

Keep out of reach of children. If swallowed, get medical help or contact a Poison Control Center right away.

Directions

- Hands must be washed and rinsed with potable water before use.
- Pump a small amount of foam into palm of hand.
- Rub thoroughly over all surfaces of both hands.
- Rub hands together briskly until dry.

Other Information

- This product must be dispensed from an adequate dispenser located a sufficient distance from processing line to prevent accidental product contamination.
- Do not contaminate water, food or feed by storage and disposal.

Inactive Ingredients

Water, Cetrimonium Chloride, Laurtrimonium Chloride, Dihydroxethyl Cocamine Oxide, Glycereth-17-Cocoate, Citric Acid

Questions?

1 -800-537-8990